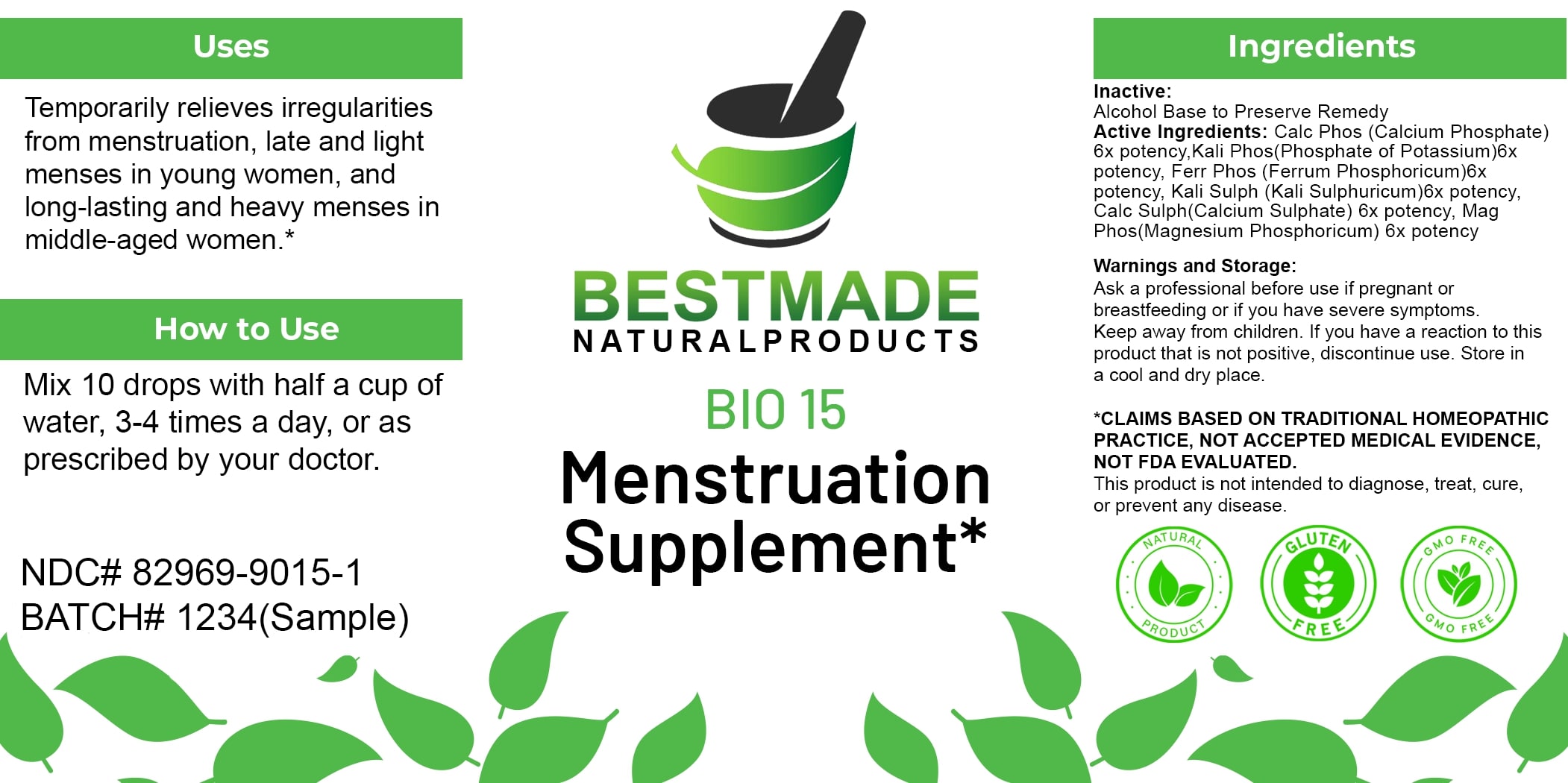 DRUG LABEL: Bestmade Natural Products BIO15
NDC: 82969-9015 | Form: LIQUID
Manufacturer: Bestmade Natural Products
Category: homeopathic | Type: HUMAN OTC DRUG LABEL
Date: 20250323

ACTIVE INGREDIENTS: MAGNESIUM PHOSPHATE, DIBASIC TRIHYDRATE 6 [hp_X]/6 [hp_X]; CALCIUM SULFATE ANHYDROUS 6 [hp_X]/6 [hp_X]; POTASSIUM PHOSPHATE, DIBASIC 6 [hp_X]/6 [hp_X]; FERROSOFERRIC PHOSPHATE 6 [hp_X]/6 [hp_X]; POTASSIUM SULFATE 6 [hp_X]/6 [hp_X]; TRIBASIC CALCIUM PHOSPHATE 6 [hp_X]/6 [hp_X]
INACTIVE INGREDIENTS: ALCOHOL 6 [hp_X]/6 [hp_X]

BIO 15 Menstruation Supplement*

DOSAGE AND ADMINISTRATION

How to Use

Mix 10 drops with half a cup of water, 3-4 times a day, or as prescribed by your doctor.

INACTIVE INGREDIENT

Ingredients

Inactive: Alcohol Base to Preserve Remedy

ACTIVE INGREDIENT

Active Ingredients: Calc Phos (Calcium Phosphate) 6x potency, Kali Phos (Phosphate of Potassium) 6x potency, Ferr Phos (Ferrum Phosphoricum) 6x potency, Kali Sulph (Kali Sulphuricum) 6x potency, Calc Sulph (Calcium Sulphate) 6x potency, Mag Phos (Magnesium Phosphoricum) 8x potency

Uses

Temporarily relieves irregularities from menstruation, late and light menses in young women, and long-lasting and heavy menses in middle-aged women.*

*CLAIMS BASED ON TRADITIONAL HOMEOPATHIC PRACTICE, NOT ACCEPTED MEDICAL EVIDENCE. NOT FDA EVALUATED.

This product is not intended to diagnose, treat, cure, or prevent any disease.

Uses

Temporarily relieves irregularities from menstruation, late and light menses in young women, and long-lasting and heavy menses in middle-aged women.*

*CLAIMS BASED ON TRADITIONAL HOMEOPATHIC PRACTICE, NOT ACCEPTED MEDICAL EVIDENCE. NOT FDA EVALUATED.

This product is not intended to diagnose, treat, cure, or prevent any disease.

KEEP OUT OF REACH OF CHILDREN

Warnings and Storage:

Ask a professional before use if pregnant or breastfeeding or if you have severe symptoms. Keep away from children. If you have a reaction to this product that is not positive, discontinue use. Store in a cool and dry place.

Warnings and Storage:

Ask a professional before use if pregnant or breastfeeding or if you have severe symptoms. Keep away from children. If you have a reaction to this product that is not positive, discontinue use. Store in a cool and dry place.

*CLAIMS BASED ON TRADITIONAL HOMEOPATHIC PRACTICE, NOT ACCEPTED MEDICAL EVIDENCE. NOT FDA EVALUATED.

This product is not intended to diagnose, treat, cure, or prevent any disease.

Entire package label